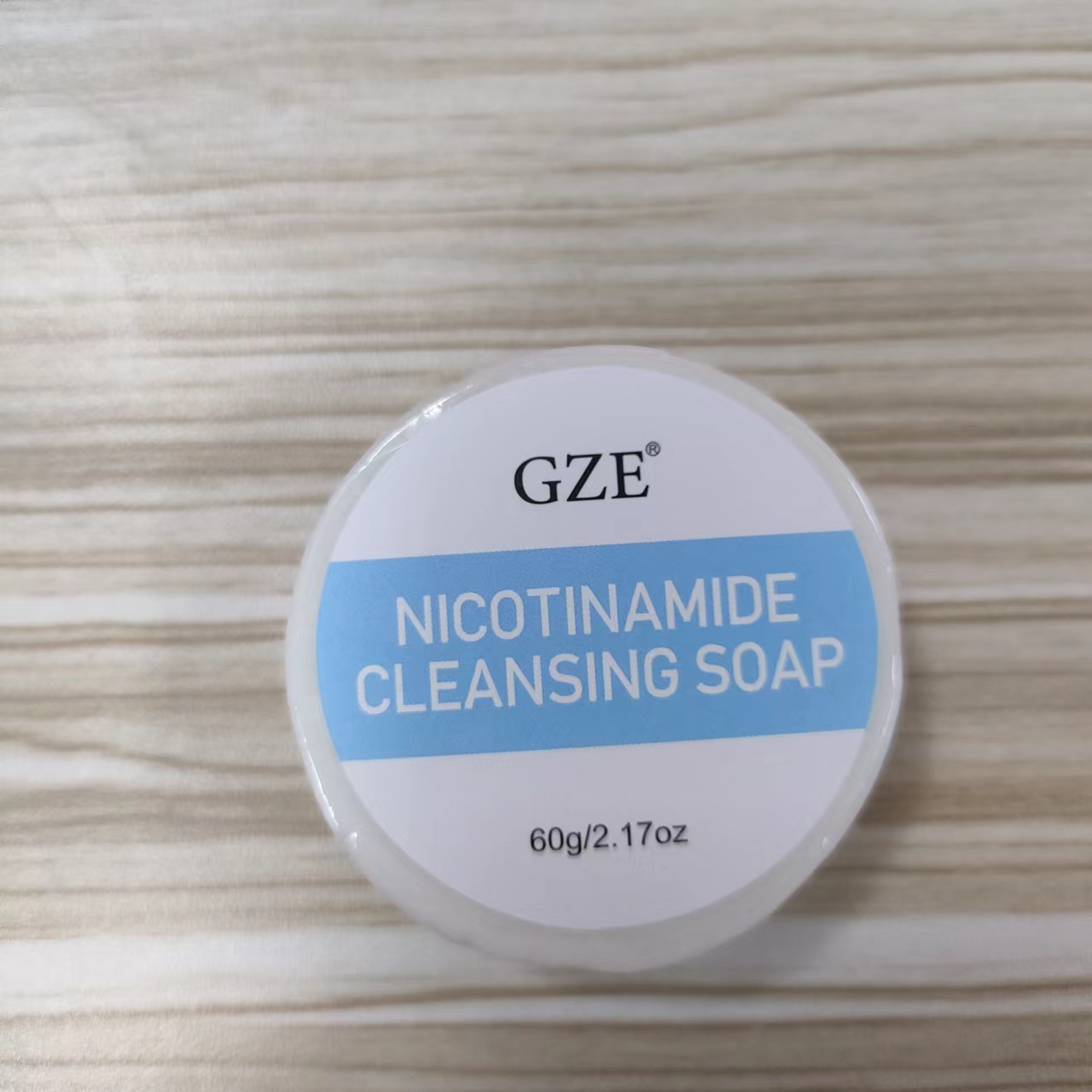 DRUG LABEL: GZE Nicotinamide CleansingSoap
NDC: 74458-165 | Form: SOAP
Manufacturer: Guangzhou Yilong Cosmetics Co., Ltd
Category: otc | Type: HUMAN OTC DRUG LABEL
Date: 20241220

ACTIVE INGREDIENTS: NIACINAMIDE 4 g/100 g
INACTIVE INGREDIENTS: DECYL GLUCOSIDE; ETHYLHEXYLGLYCERIN; DISODIUM COCOAMPHODIACETATE; SODIUM HYALURONATE; POTASSIUM SORBATE; DISODIUM COCOYL GLUTAMATE; SODIUM ASCORBYL PHOSPHATE; XANTHAN GUM; PHENOXYETHANOL; CITRIC ACID; AQUA; MYRCIARIA DUBIA FRUIT; TOCOPHEROL; GLYCERIN

GZE NICOTINAMIDE CLEANSING SOAP

ACTIVE INGREDIENT

Niacinamide 4%

INACTIVE INGREDIENT

Aqua

Disodium Cocoyl Glutamate

Glycerin

Disodium Cocoamphodiacetate

Decyl Glucoside

Xanthan Gum

Sodium Hyaluronate

Myrciaria Dubia Fruit Extract

Sodium Ascorbyl Phosphate

Phenoxyethanol

Citric Acid

Ethylhexylglycerin

Potassium Sorbate

Tocopherol

PURPOSE

Cleansing

INDICATIONS AND USAGE

Lather onto wet or dry skin. Rinse and follow with
serum and moisturizer. After aproduct is opened, it should be used within
two years.

WARNINGS

For external use only.

Stop use and ask a doctor if rash occurs.

Do not use on damaged or broken skin.

When using this product keep out of eyes. Rinse with water to remove.

Keep out of reach of children. If swallowed, get medical help or contact a Poison Control Center right away.

DOSAGE AND ADMINISTRATION

Lather onto wet or dry skin. Rinse and follow with
serum and moisturizer. After aproduct is opened, it should be used within
two years.